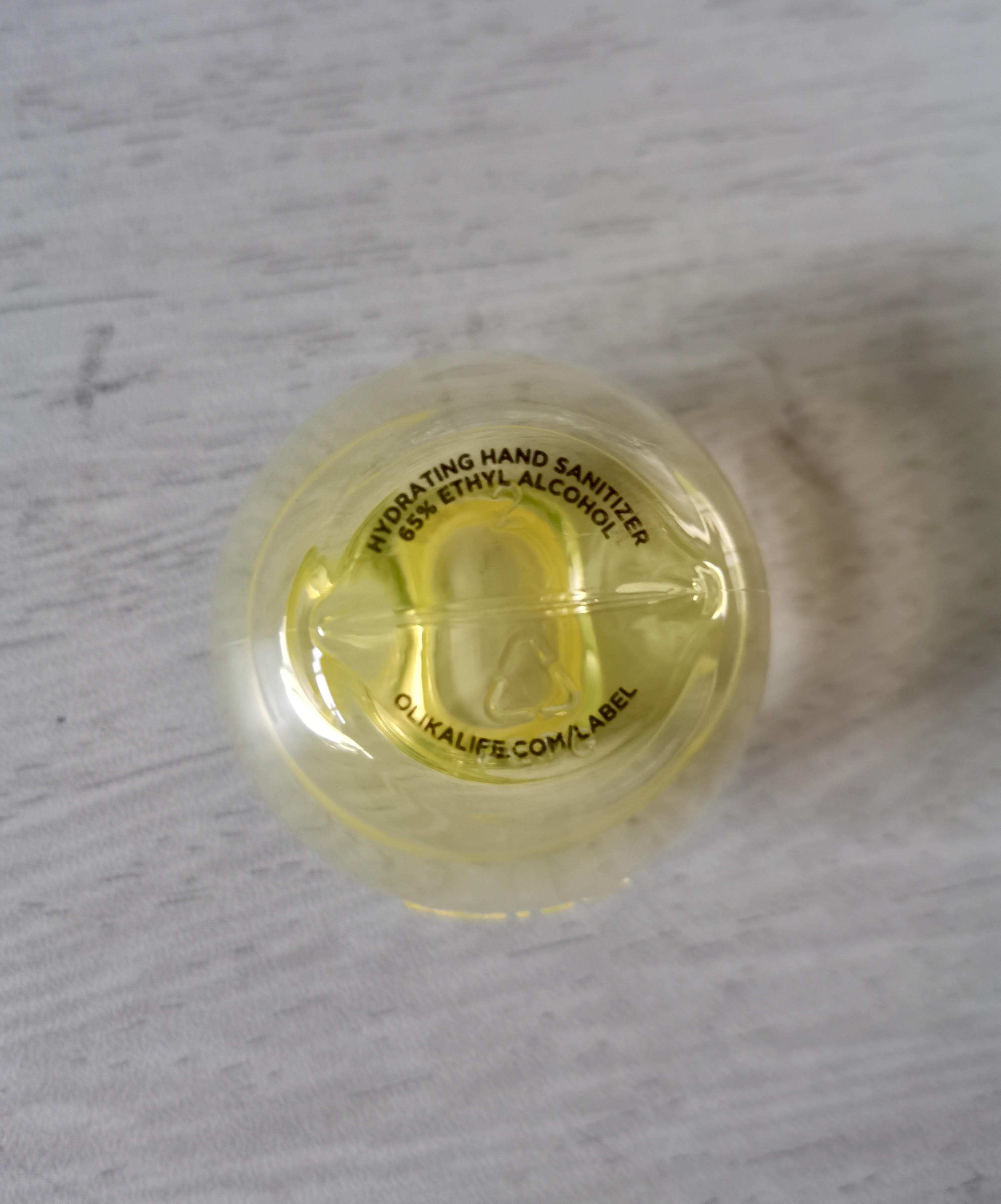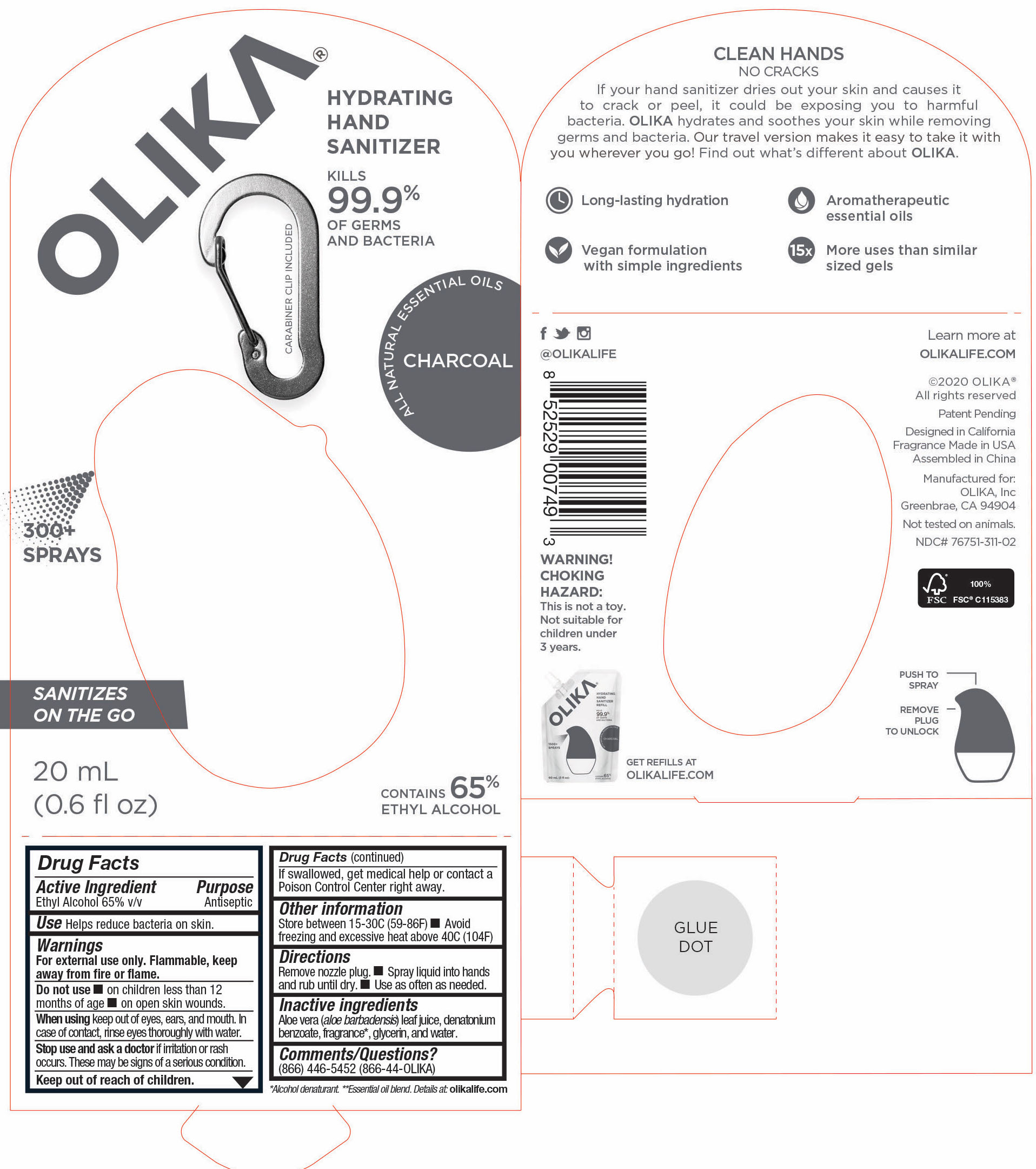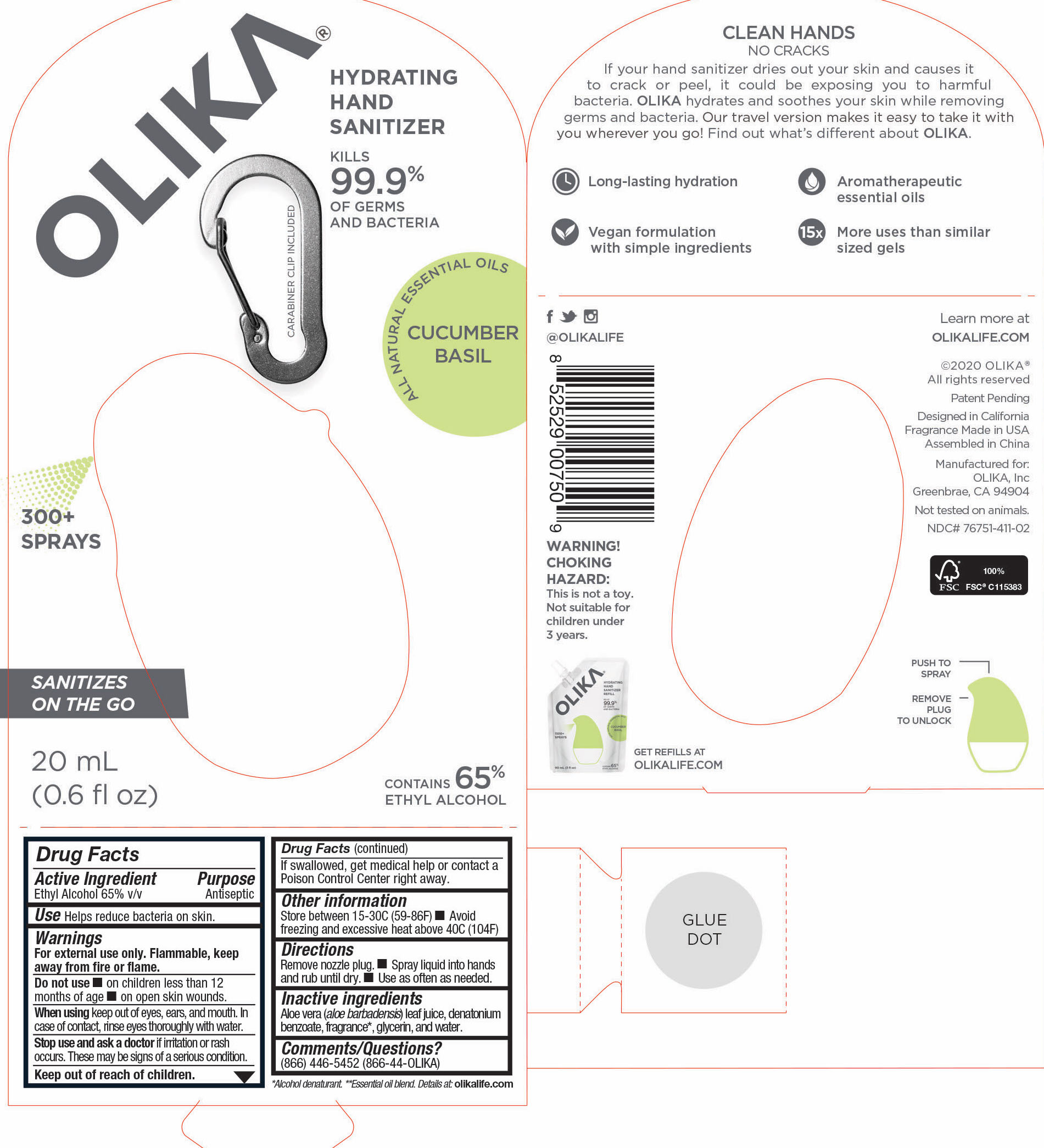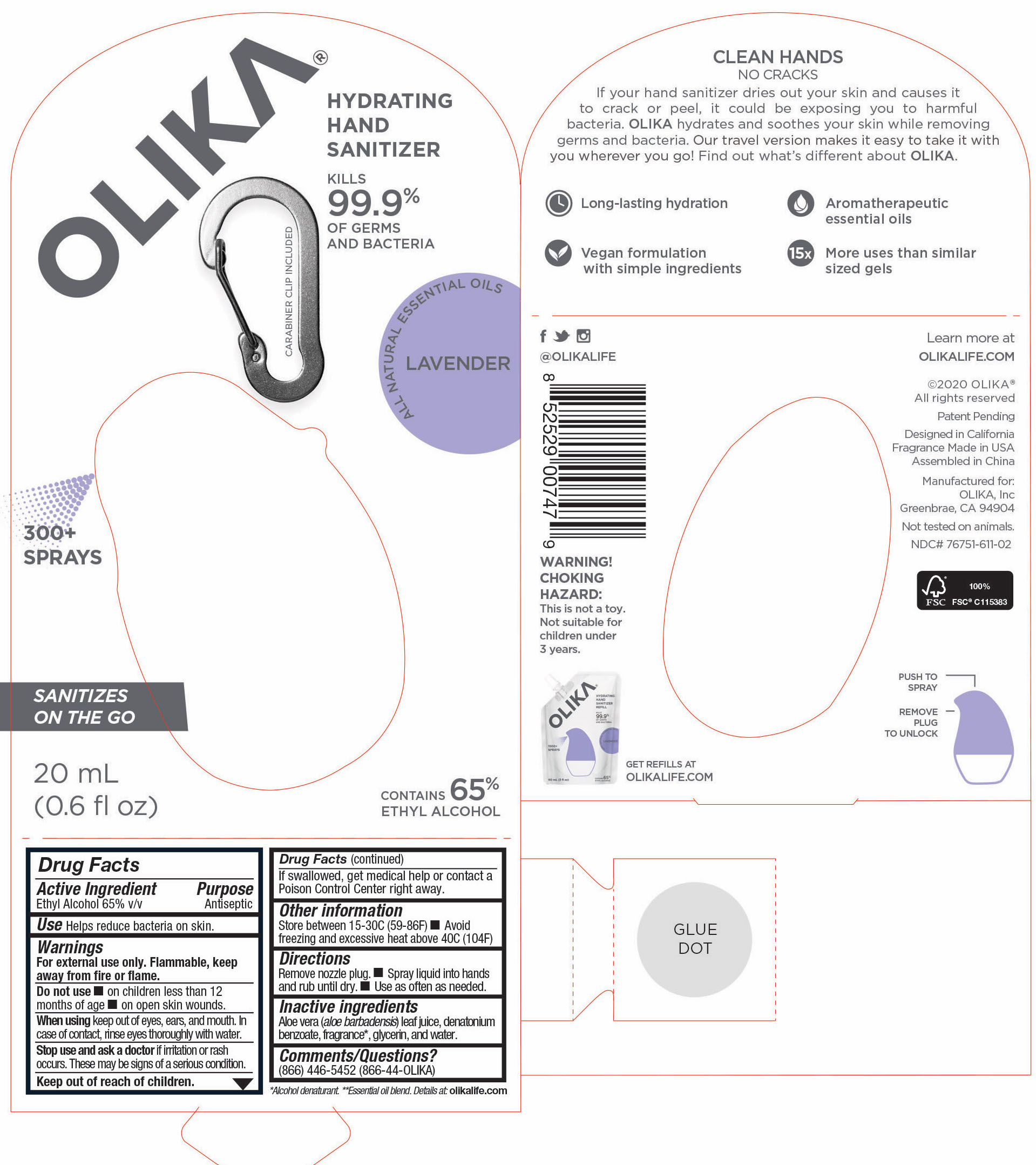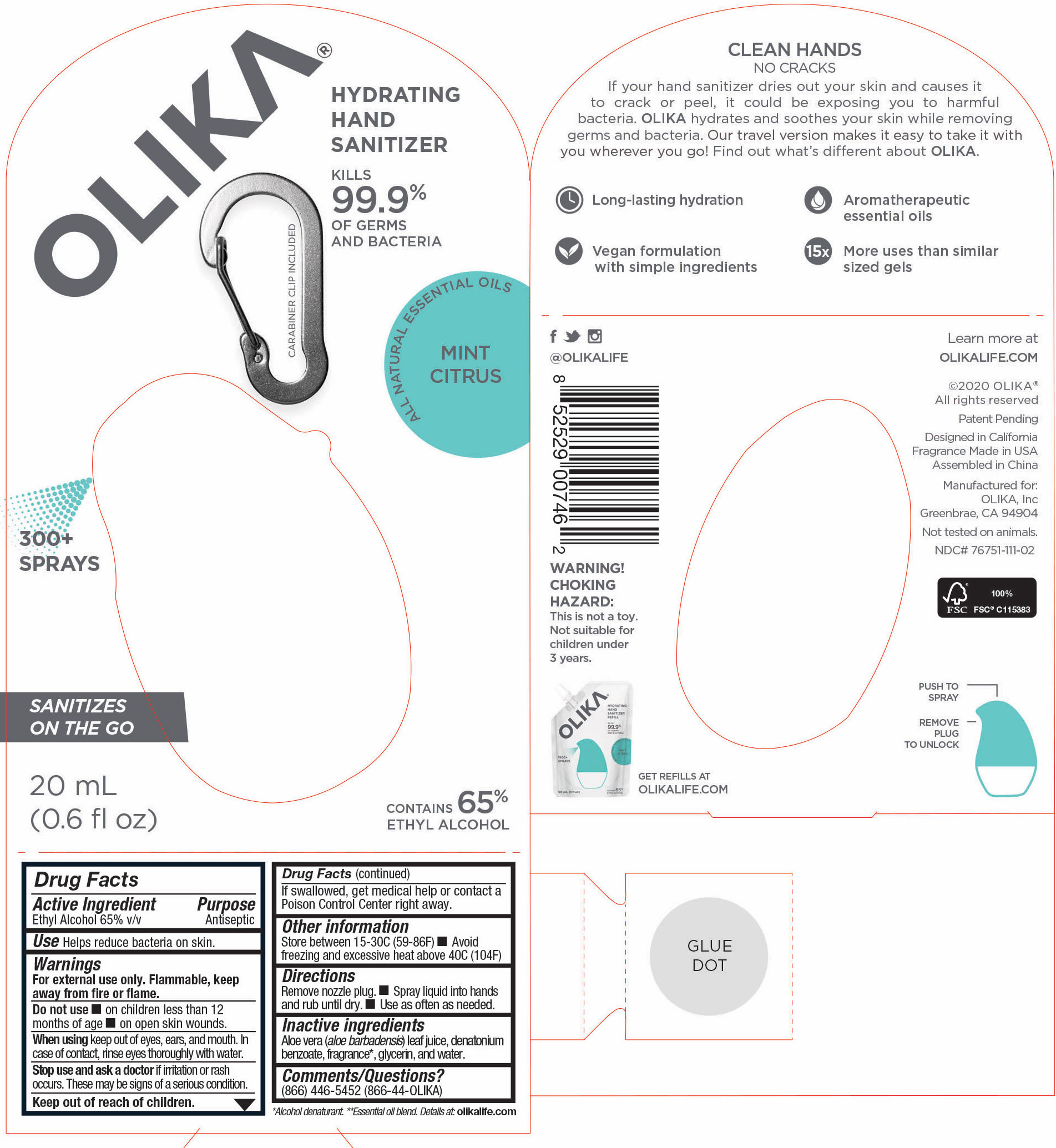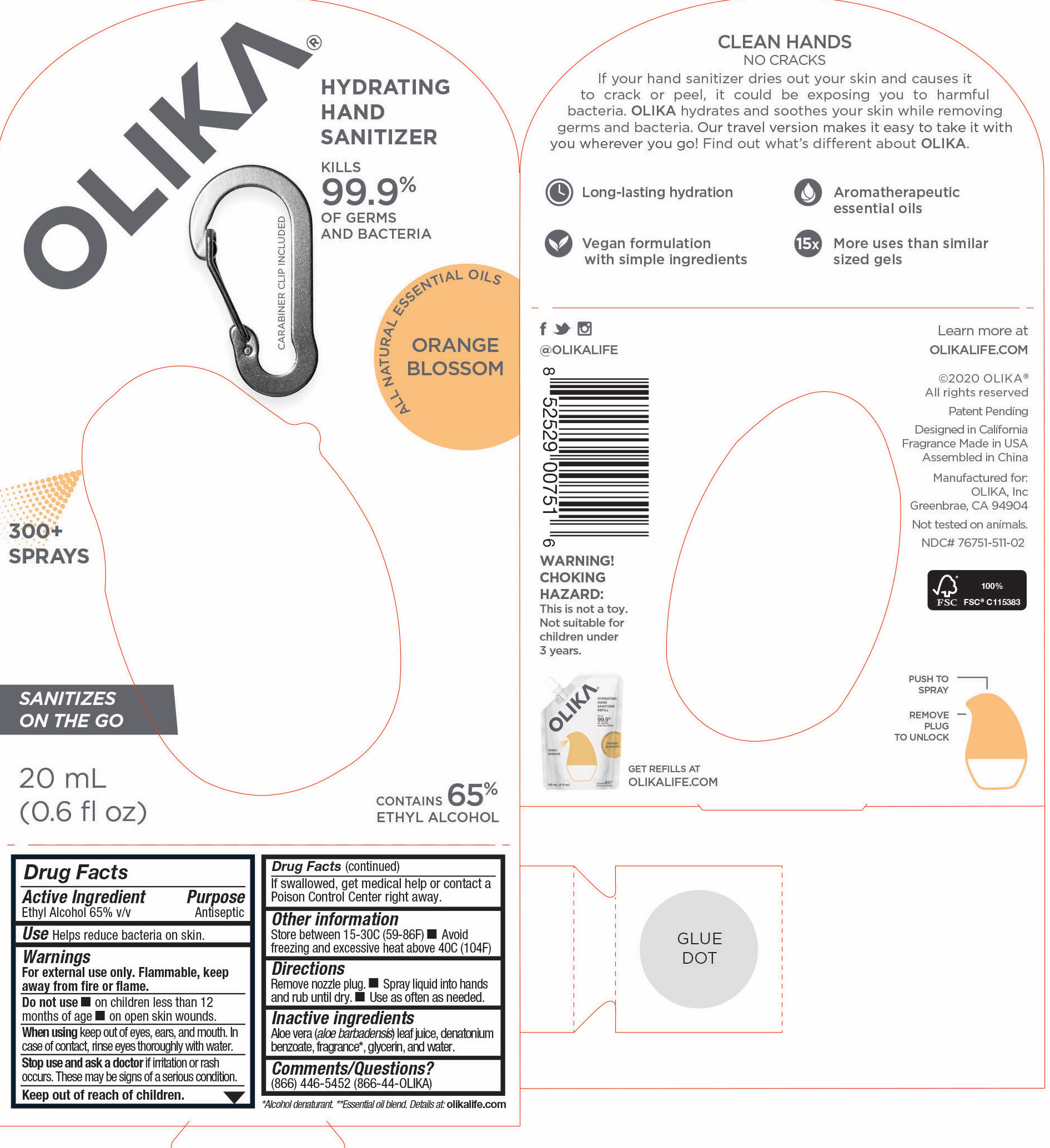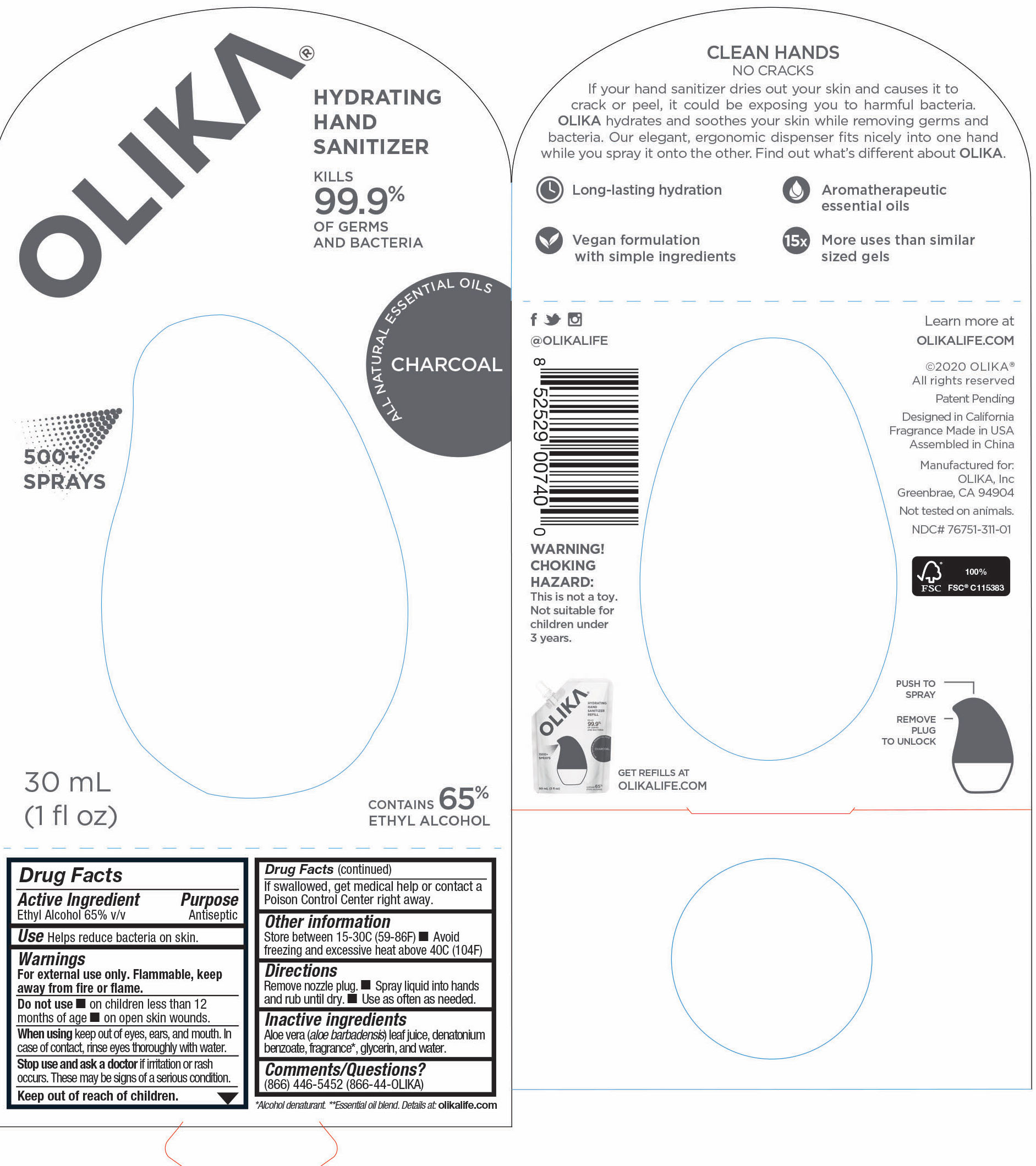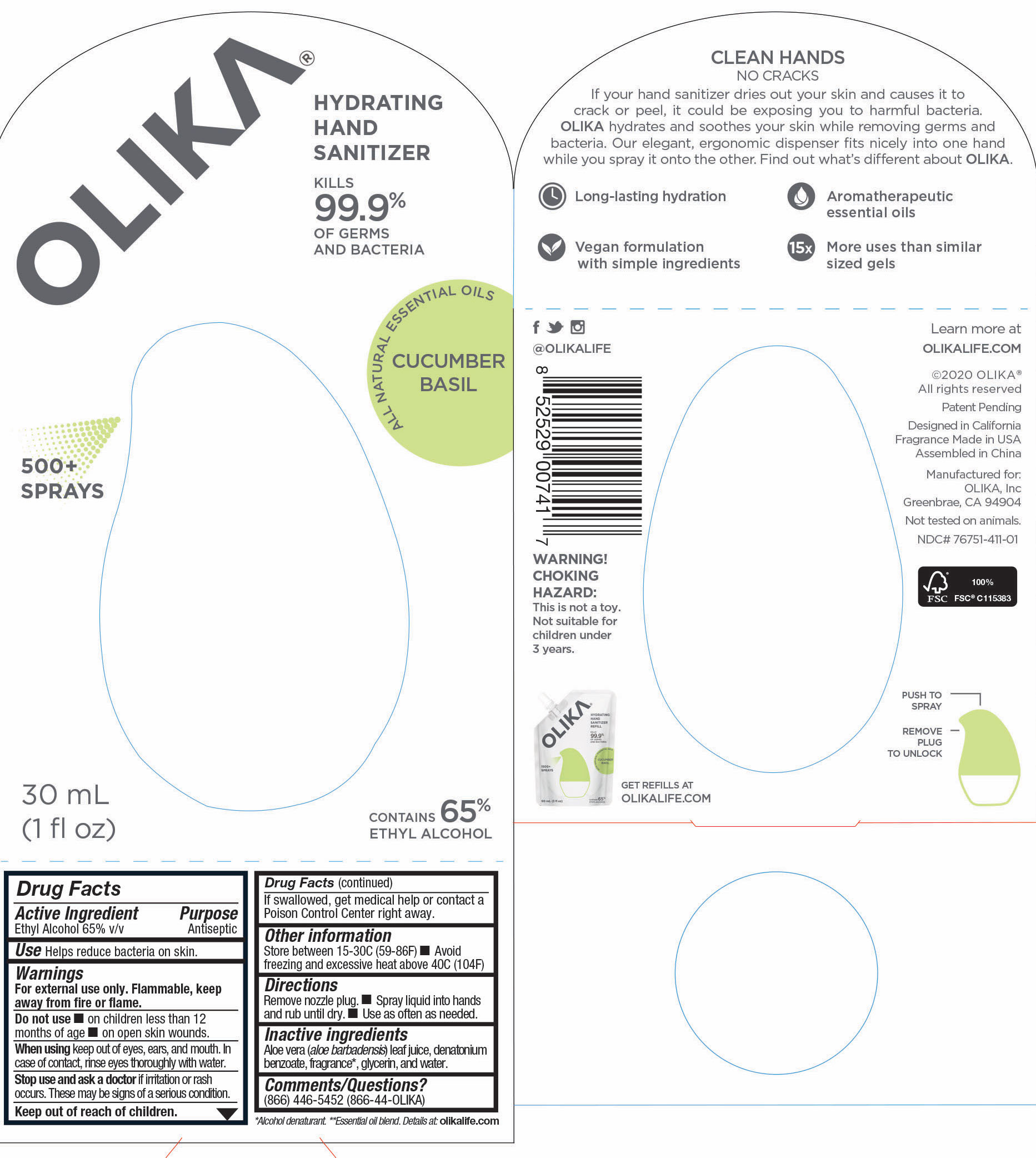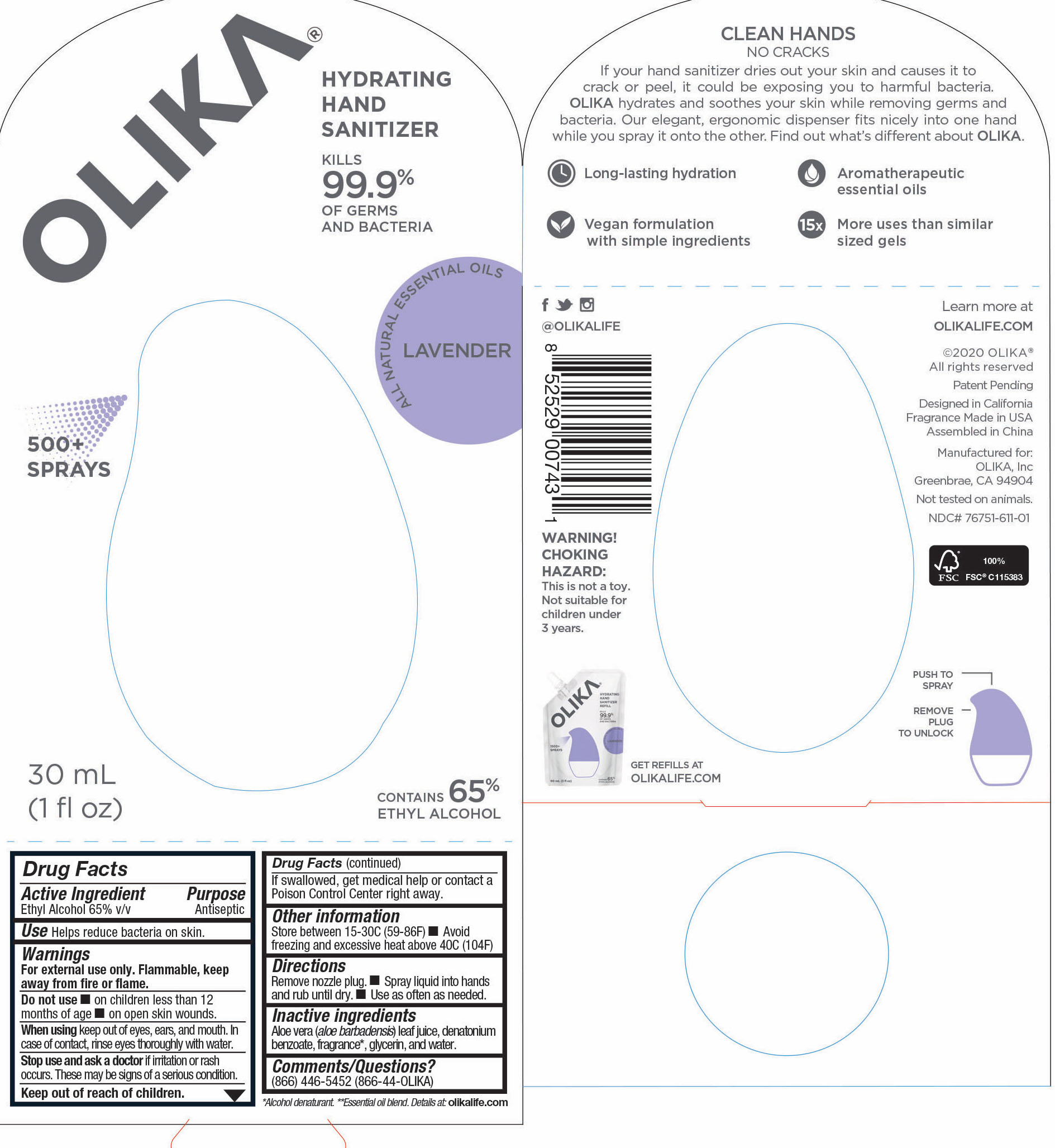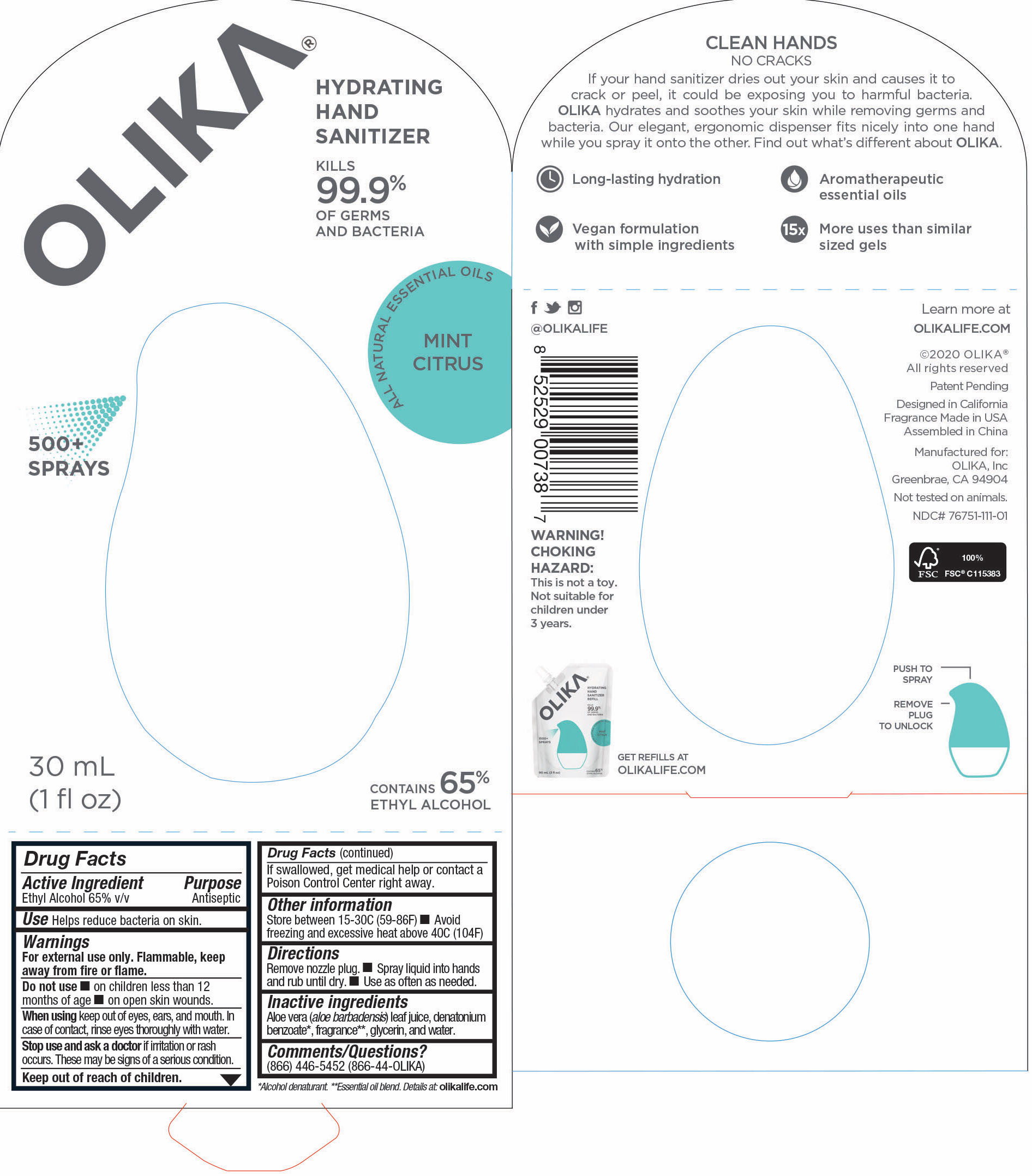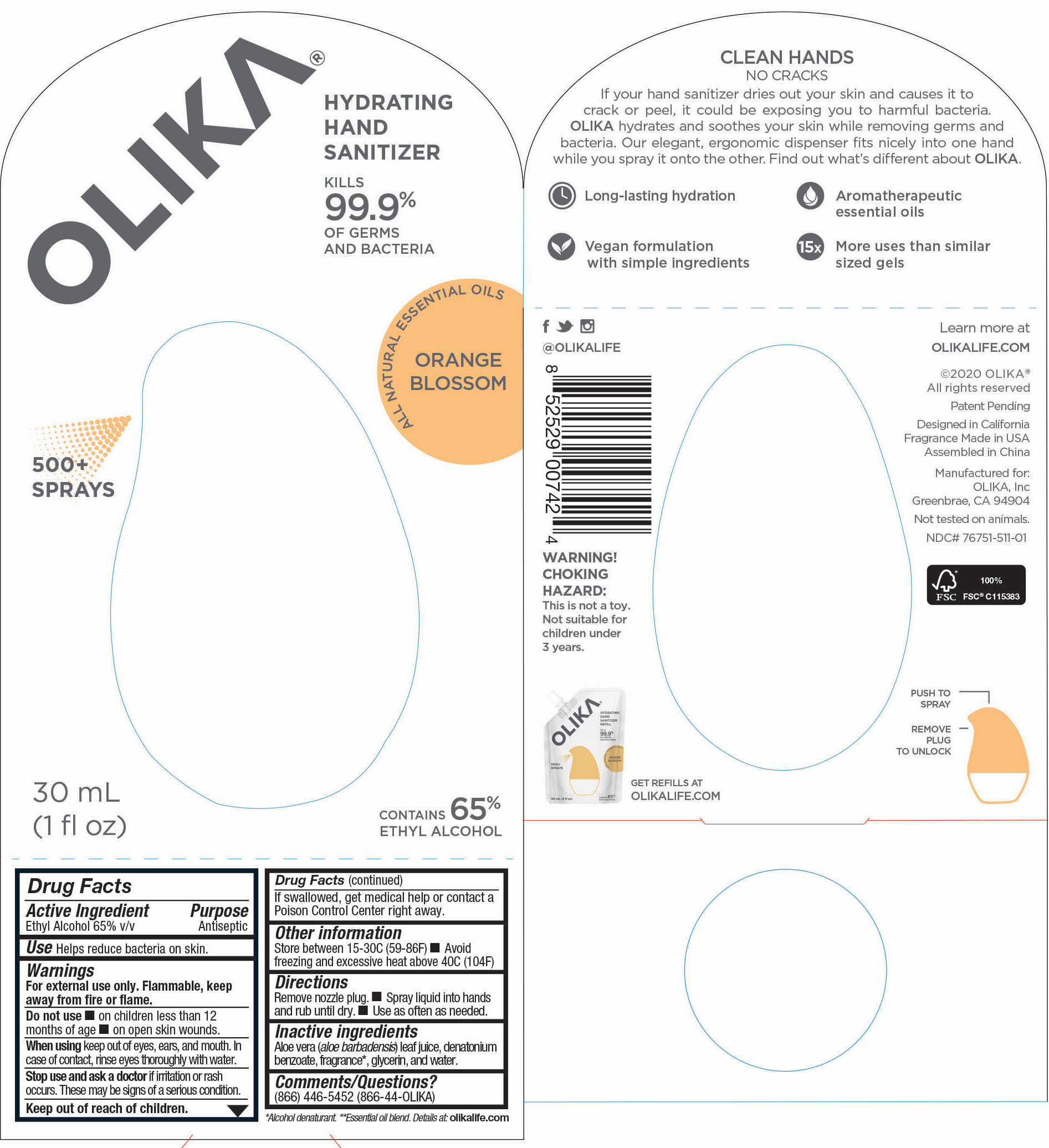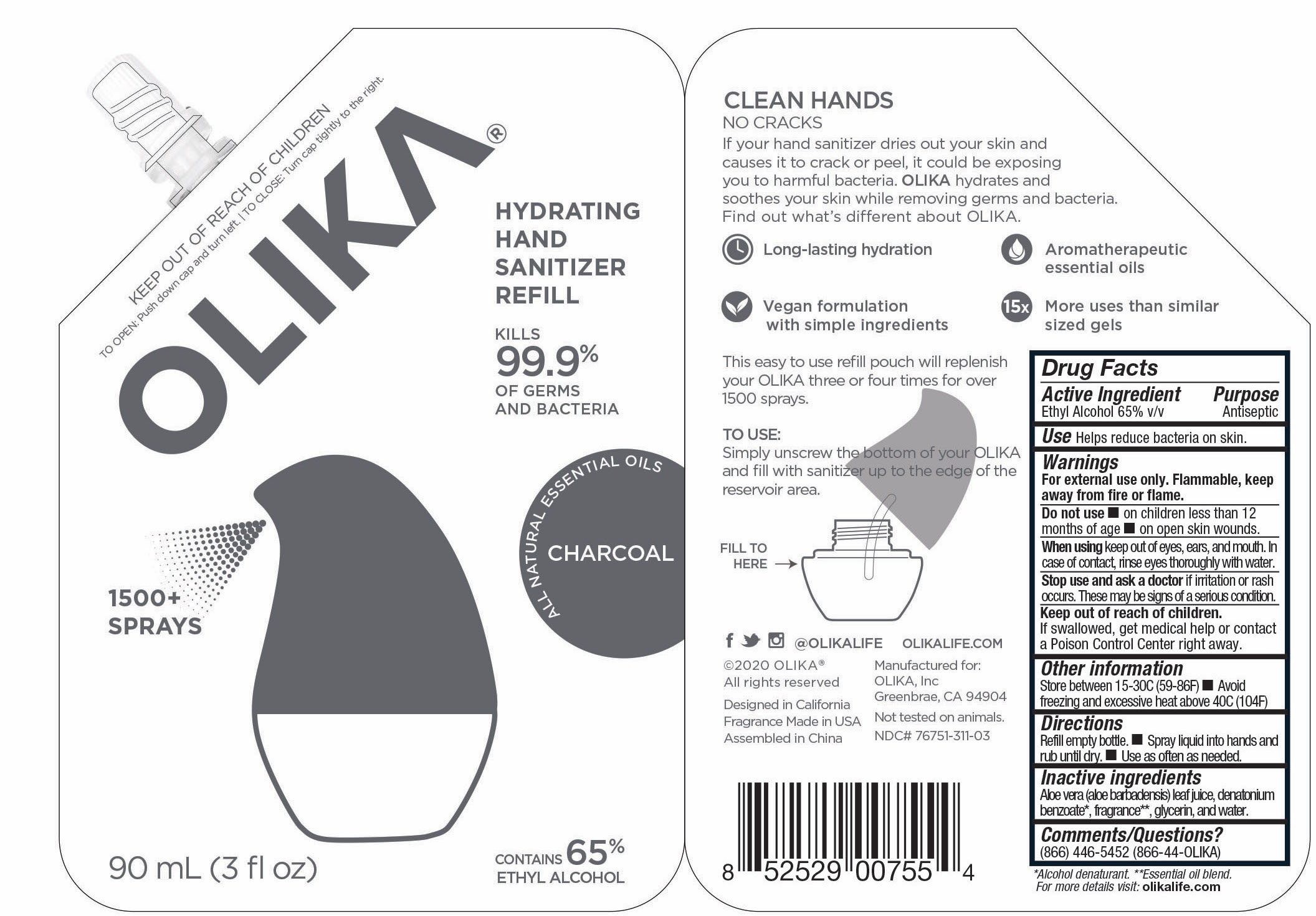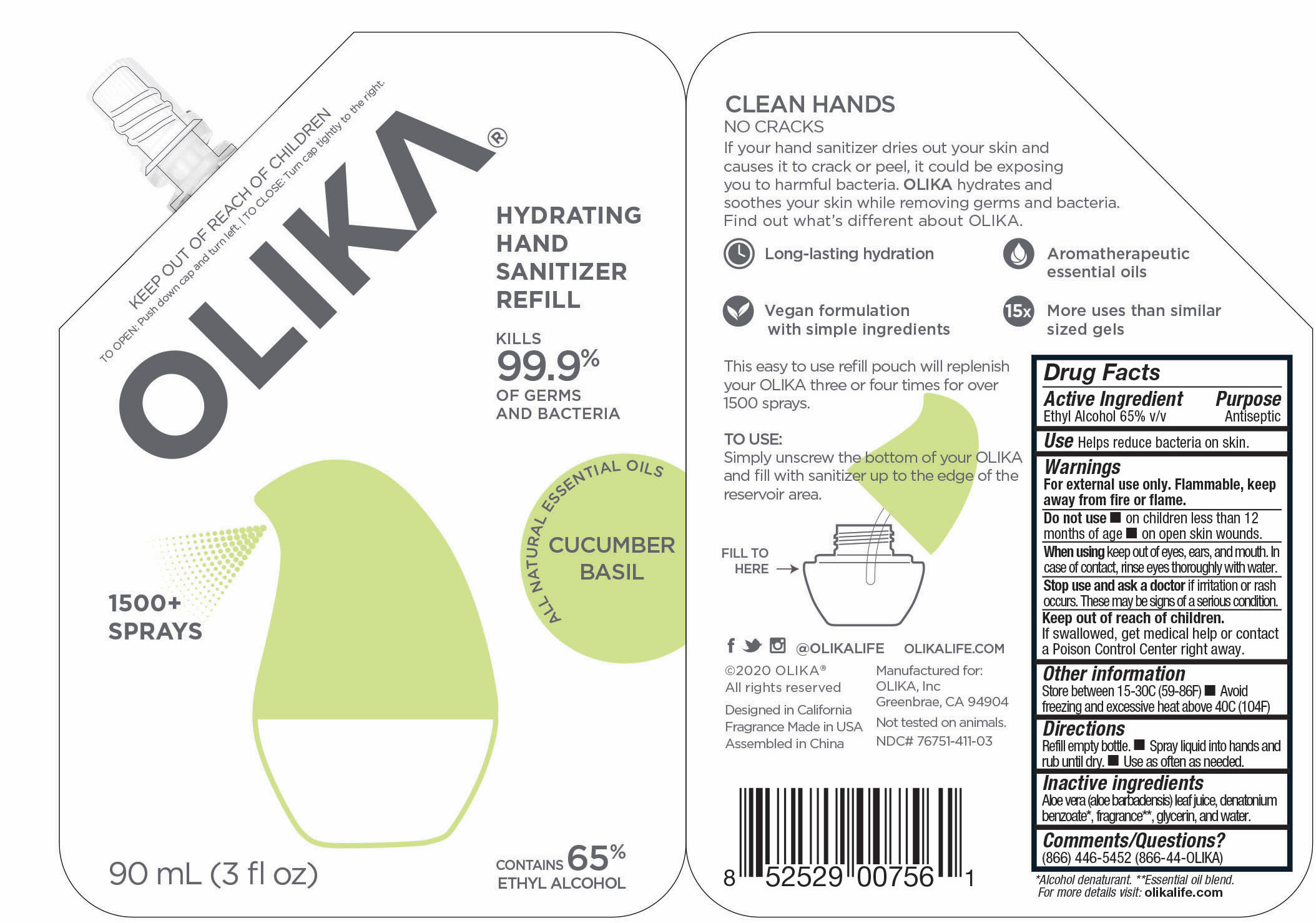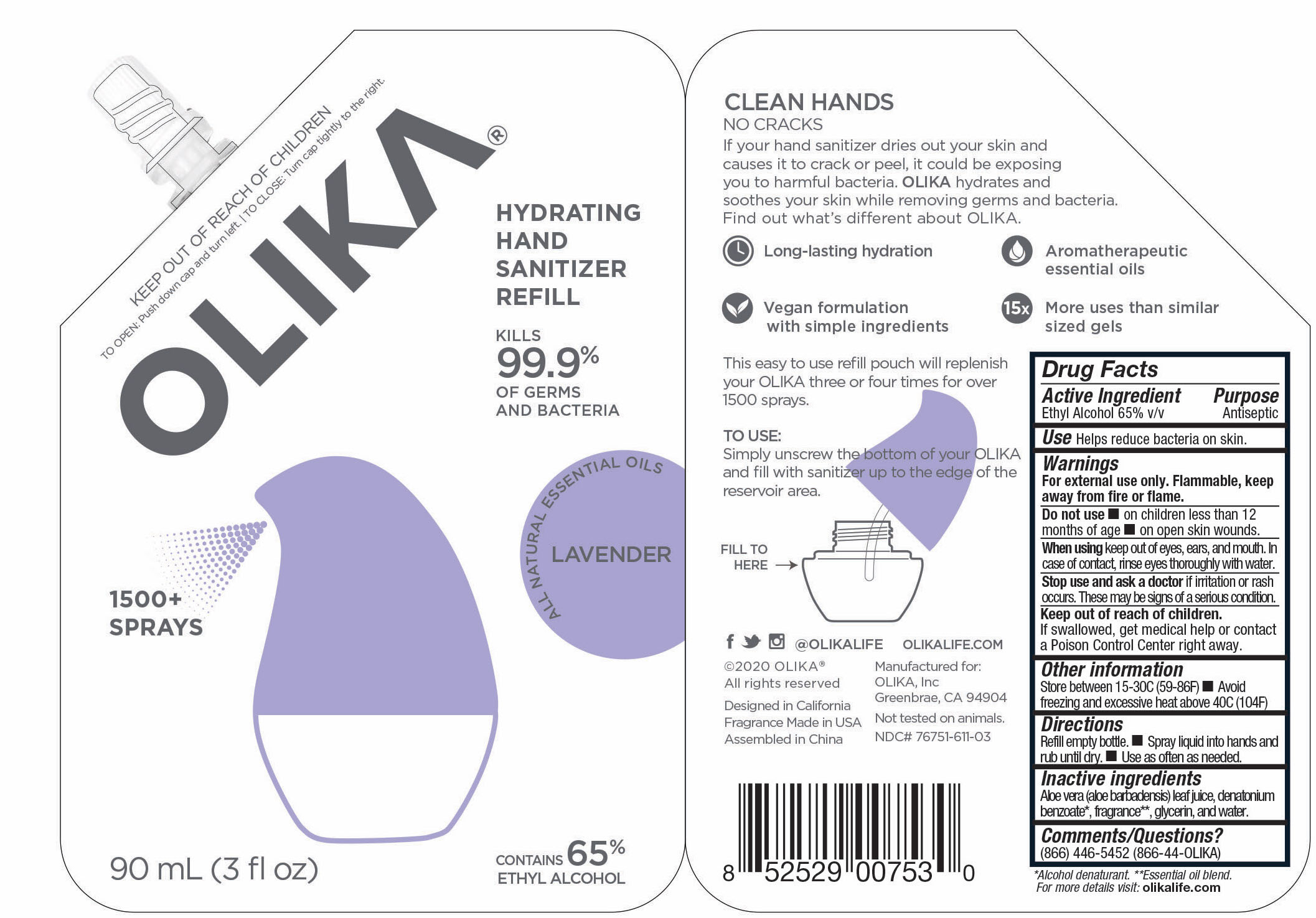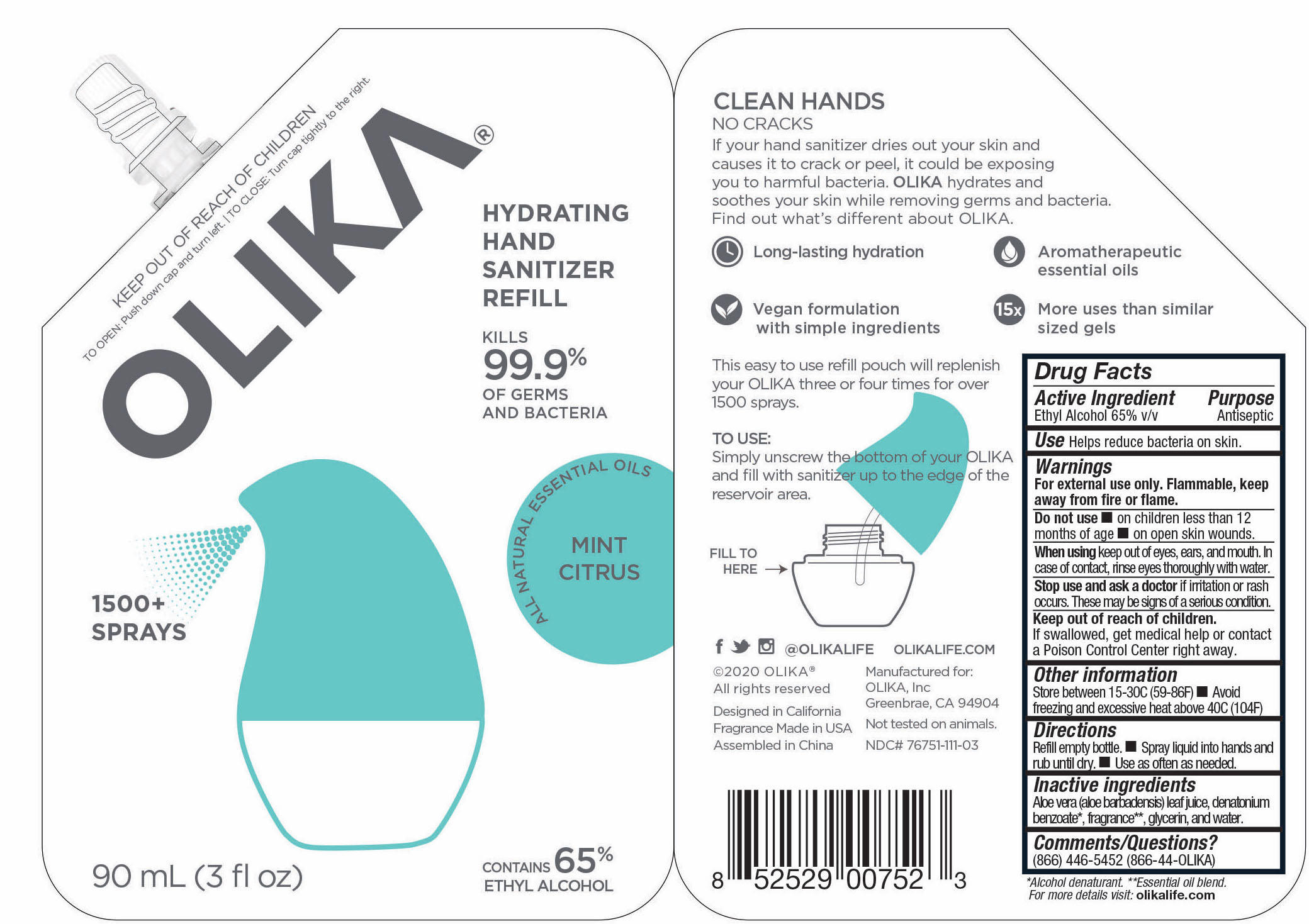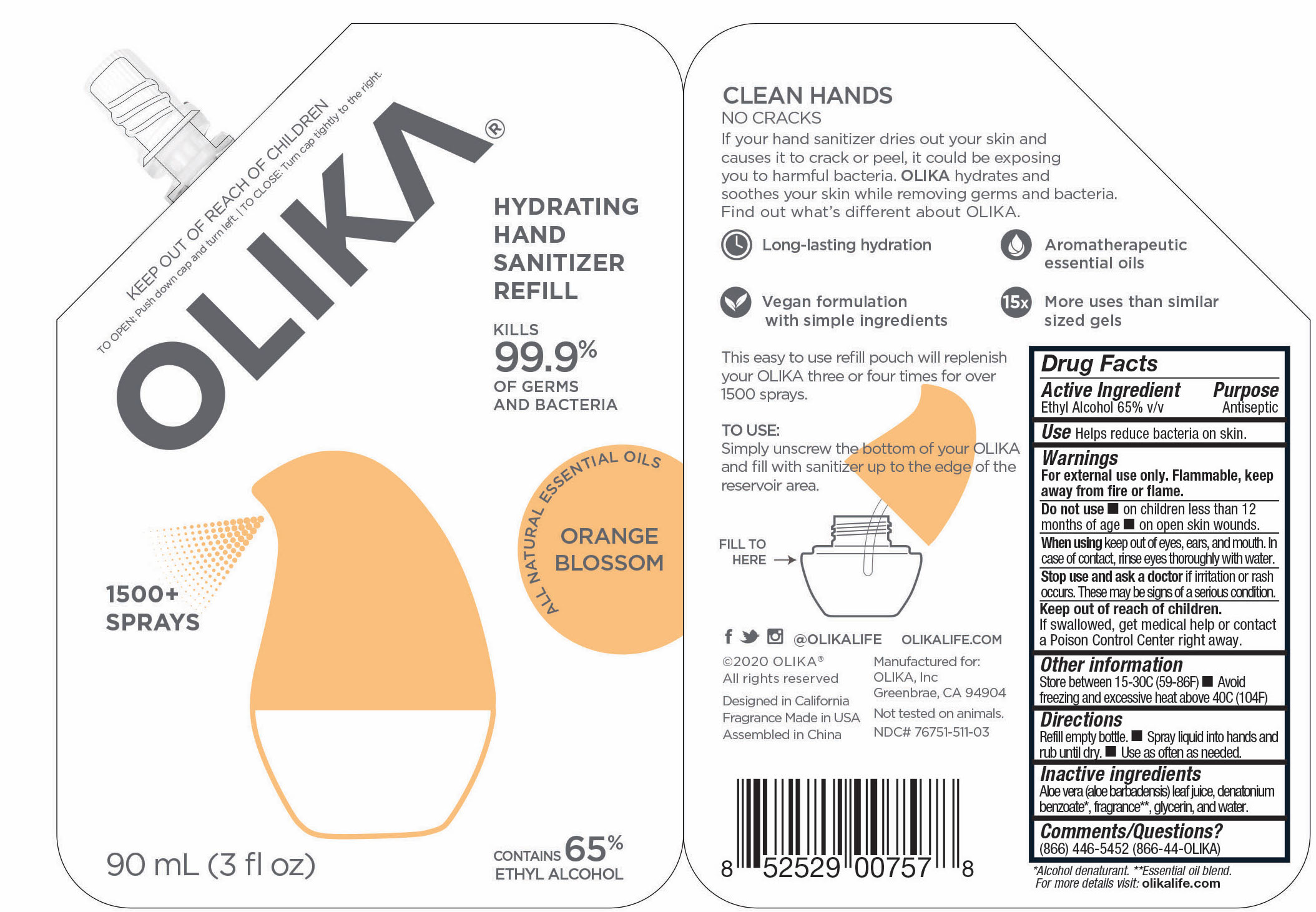 DRUG LABEL: OLIKA Hand Sanitizer Orange Blossom
NDC: 76751-511 | Form: LIQUID
Manufacturer: Olika Inc.
Category: otc | Type: HUMAN OTC DRUG LABEL
Date: 20211210

ACTIVE INGREDIENTS: ALCOHOL 65 mL/100 mL
INACTIVE INGREDIENTS: PIPERONAL 0.0003 mL/100 mL; PELARGONIUM GRAVEOLENS FLOWER OIL 0.0007 mL/100 mL; CITRUS AURANTIUM FRUIT OIL 0.0005 mL/100 mL; TRIETHYL CITRATE 0.3368 mL/100 mL; LINALOOL, (-)- 0.017 mL/100 mL; .ALPHA.-TERPINEOL 0.0048 mL/100 mL; PALMAROSA OIL 0.0096 mL/100 mL; GLYCERIN 4.2 mL/100 mL; ALOE VERA LEAF 0.25 mL/100 mL; WATER 30.05 mL/100 mL; MALTOL 0.0003 mL/100 mL; .DELTA.-DODECALACTONE 0.0002 mL/100 mL; BENZYL SALICYLATE 0.0013 mL/100 mL; LITSEA OIL 0.0032 mL/100 mL; ORANGE OIL 0.0028 mL/100 mL; 2,6-DIMETHYL-5-HEPTENAL 0.0002 mL/100 mL; .DELTA.-DECALACTONE 0.0013 mL/100 mL; PHENYLETHYL ALCOHOL 0.0006 mL/100 mL; VANILLIN 0.0005 mL/100 mL; CARDAMOM OIL 0.0002 mL/100 mL; METHYL ANTHRANILATE 0.001 mL/100 mL; CITRUS SINENSIS LEAF 0.0084 mL/100 mL; CANANGA ODORATA FLOWER 0.0029 mL/100 mL; .GAMMA.-OCTALACTONE 0.0005 mL/100 mL; BERGAMOT OIL 0.0112 mL/100 mL; POGOSTEMON CABLIN LEAF OIL 0.0006 mL/100 mL; .GAMMA.-DECALACTONE 0.0006 mL/100 mL; MANDARIN OIL 0.0016 mL/100 mL; CLOVE LEAF OIL 0.0026 mL/100 mL; CITRUS SINENSIS FLOWER OIL 0.0888 mL/100 mL; ALLYL HEXANOATE 0.0013 mL/100 mL; LEMON OIL 0.0002 mL/100 mL

OLIKA Hand Sanitizers in 5 scents in 3 sizes each 20 mL, 30 mL, 90 mL

These products are hand sanitizers manufactured according to the 1994 tentative final monograph for antiseptics with additional guidance taken from subsequent rule makings and guidances.

The hand sanitizer is manufactured using only the following United States Pharmacopoeia (USP) grade ingredients in the preparation of the product (percentage in final product formulation).

1. Alcohol (ethanol) (USP or Food Chemical Codex (FCC) grade) (65%, volume/volume (v/v)) in an aqueous solution denatured according to Alcohol and Tobacco Tax and Trade Bureau regulations in 27 CFR part 20.
2. Glycerol (4.2% v/v).
3. Aloe Barbadensis Leaf Extract.
4. Sterile distilled water or boiled cold water.
5. Fragrance

The finished product formulation underwent third party efficacy testing (kill study) to confirm efficacy and product potency.

The hand sanitizer come in 6 different scents. Fragrance free (submitted separately NDC 76751-211), Lavender (NDC 76751-611), Orange Blossom (NDC 76751-511), Mint Citrus (NDC 76751-111), Charcoal (NDC 76751-311) and Cucumber Basil (NDC 76751-411).

Active Ingredient(s)

Alcohol 65% v/v. Purpose: Antiseptic

Purpose

Antiseptic, Hand Sanitizer

Warnings

For external use only. Flammable. Keep away from heat or flame

Do not use

- in children less than 2 months of age
- on open skin wounds

When using this product keep out of eyes, ears, and mouth. In case of contact with eyes, rinse eyes thoroughly with water.
Stop use and ask a doctor if irritation or rash occurs. These may be signs of a serious condition.
Keep out of reach of children. If swallowed, get medical help or contact a Poison Control Center right away.

Stop use and ask a doctor if irritation or rash occurs. These may be signs of a serious condition.

Keep out of reach of children. If swallowed, get medical help or contact a Poison Control Center right away.

Other information

- Store between 15-30C (59-86F)
- Avoid freezing and excessive heat above 40C (104F)

Use

Helps reduce bacteria on skin.

Directions

- Remove nozzel bead.
- Spray liquid in hands and rub until dry.
- Use as often as needed.

Inactive Ingredients

Inactive Ingredients for NDCs 76751-111-01; 76751-311-01; 76751-411-01; 76751-511-01; 76751-611-01

- Aloe Barbadensis Leaf Extract
- Fragrance (Essential Oil Blend)
- Glycerin
- Water

Primary container spray bottle bottom label

Bottom label for primary container spray bottle for all scents:

76751-411-01 Prinicipal Display Panel and information panel image

76751-411-01 30 mL

76751-111-01 Prinicipal Display Panel and information Panel

30 mL NDC 76751-111-01

76751-311-01 Image Principal Display Panel & Information Panel

30 mL NDC 76751-311-01

76751-511-01 Principal Display panel and information panel

30mL NDC 76751-511-01

76751-111-02 Principal Display and Information Panel

20 mL NDC 76751-111-02

76751-311-02 Principal Display and Information Panel

20mL NDC 76751-311-02

76751-611-02 PRINCIPAL DISPLAY PANEL AND INFORMATION LABEL

20 mL NDC 76751-611-02

76751-411-02 PRINCIPAL DISPLAY PANEL AND INFORMATION PANEL

20 mL NDC 76751-411-02

76751-111-03 PRINCIPAL DISCPLAY PANEL AND INFORMATION PANEL

90 mL NDC 76751-111-03

76751-611-03 PRINCIPAL DISPLAY PANEL AND INFORMATION PANEL

90 mL NDC 76751-611-03

76751-311-03 PRINCIPAL DISPLAY PANEL AND INFORMATION PANEL

90 mL NDC 76751-311-03

76751-411-03 PRINCIPAL DISPLAY PANEL AND INFORMATION PANEL

90 mL NDC 76751-411-03

76751-511-03 PRINCIPAL DISPLAY PANEL AND INFORMATON PANEL

90 mL NDC 76751-511-03

76751-611-01 PRINCIPAL DISPLAY PANEL AND INFORMATION PANEL

30mL NDC 76751-611-01

76751-511-02 PRINCIPAL DISPLAY PANEL AND INFORMATION PANEL

20 mL NDC 76751-511-02